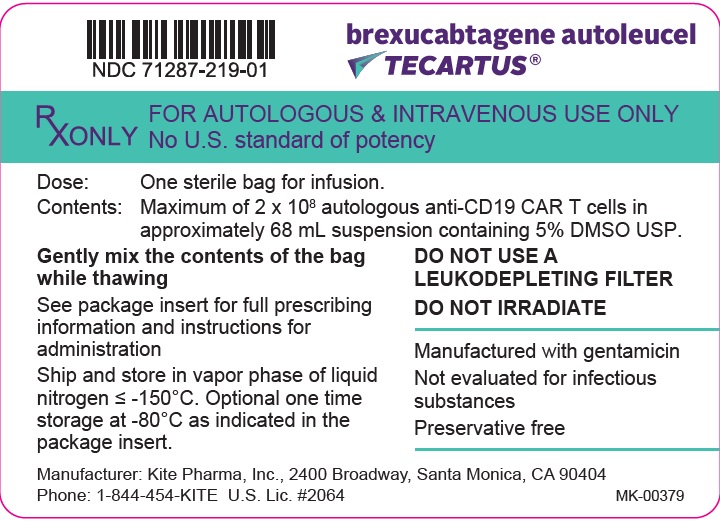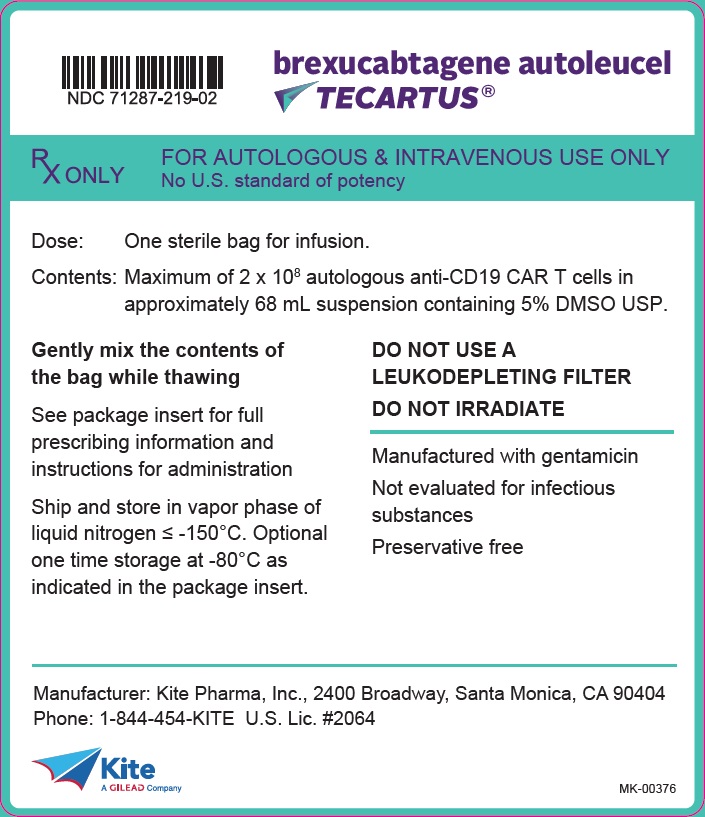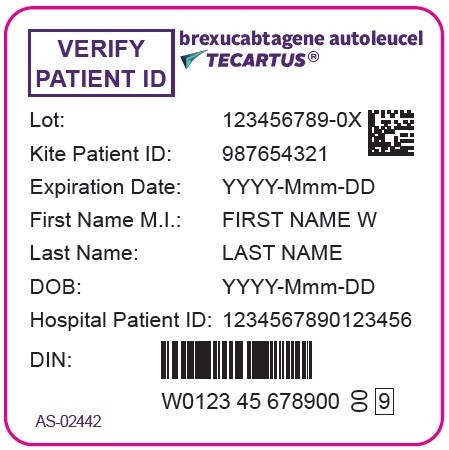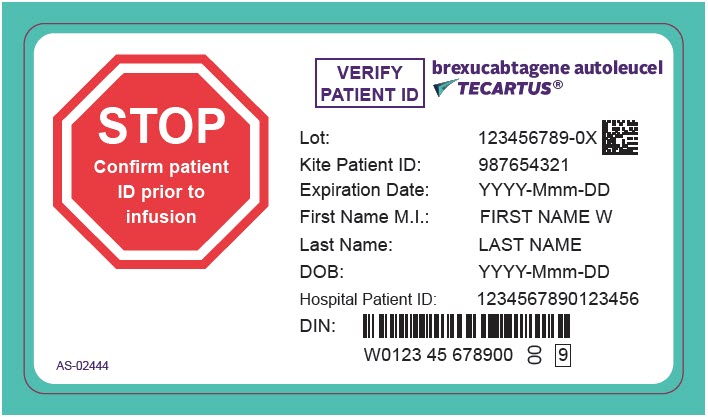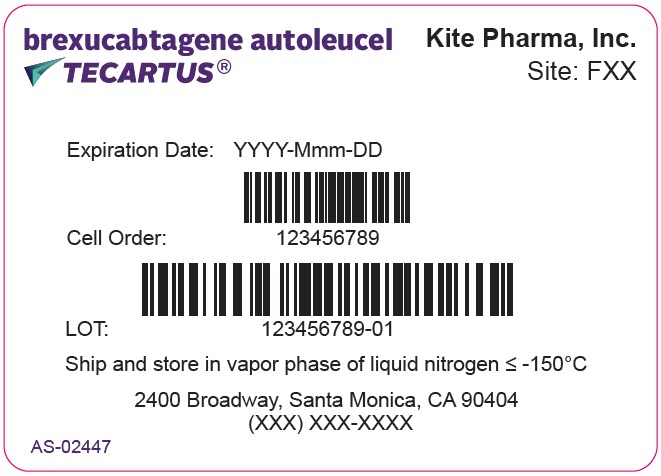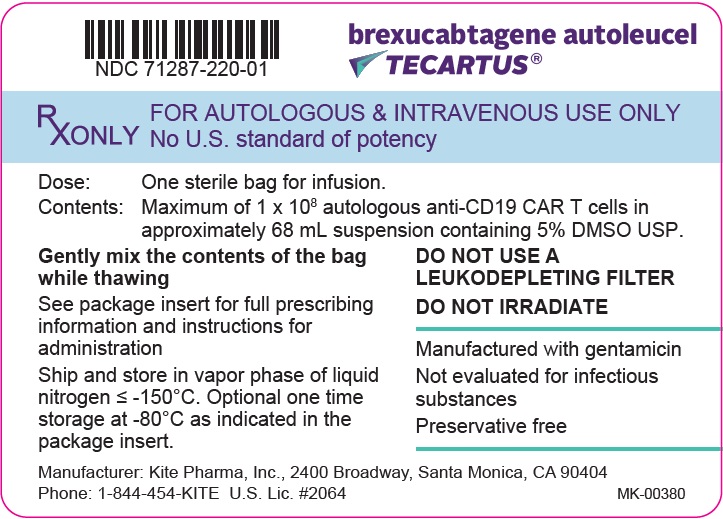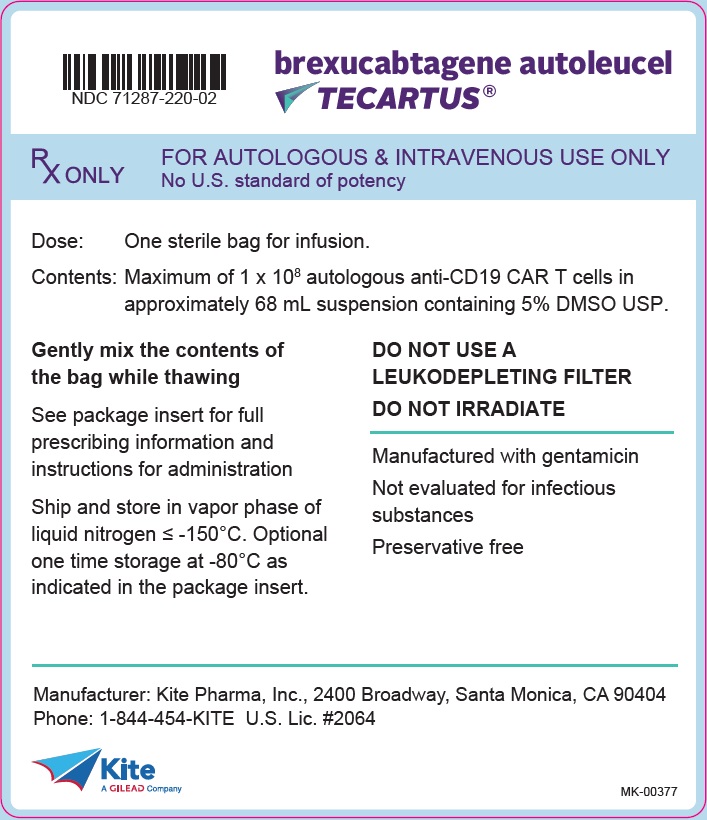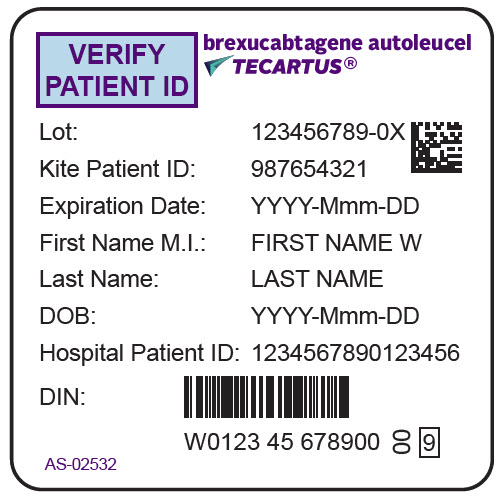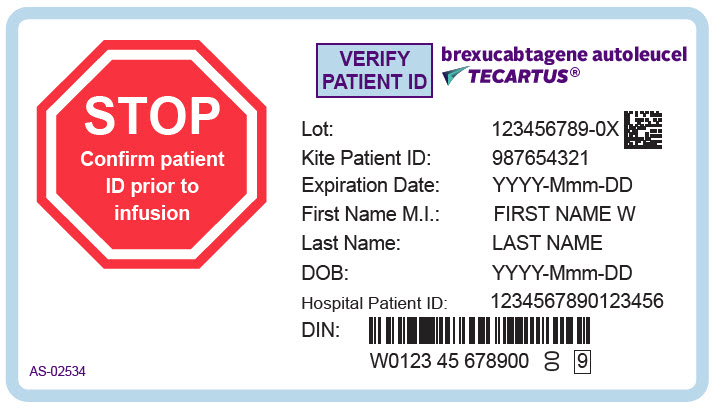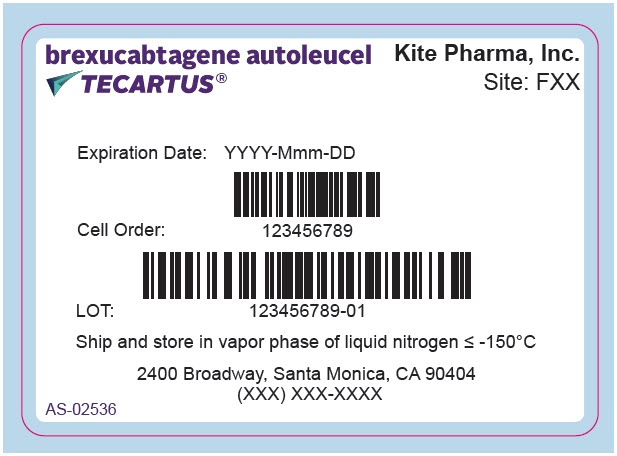 DRUG LABEL: TECARTUS
NDC: 71287-219 | Form: SUSPENSION
Manufacturer: Kite Pharma, Inc.
Category: other | Type: CELLULAR THERAPY
Date: 20251021

ACTIVE INGREDIENTS: BREXUCABTAGENE AUTOLEUCEL 2000000 1/68 mL
INACTIVE INGREDIENTS: DIMETHYL SULFOXIDE; ALBUMIN HUMAN

HIGHLIGHTS OF PRESCRIBING INFORMATION

These highlights do not include all the information needed to use TECARTUS safely and effectively. See full prescribing information for TECARTUS.
TECARTUS® (brexucabtagene autoleucel) suspension for intravenous infusion
Initial U.S. Approval: 2020

WARNING: CYTOKINE RELEASE SYNDROME, NEUROLOGIC TOXICITIES, and SECONDARY HEMATOLOGICAL MALIGNANCIES

See full prescribing information for complete boxed warning.

- Cytokine Release Syndrome (CRS), including life-threatening reactions, occurred in patients receiving TECARTUS. Do not administer TECARTUS to patients with active infection or inflammatory disorders. Treat severe or life-threatening CRS with tocilizumab or tocilizumab and corticosteroids (2.2, 2.3, 5.1).
- Neurologic toxicities, including life-threatening reactions, occurred in patients receiving TECARTUS, including concurrently with CRS or after CRS resolution. Monitor for neurologic toxicities after treatment with TECARTUS. Provide supportive care and/or corticosteroids, as needed (2.2, 2.3, 5.2).
- T cell malignancies have occurred following treatment of hematologic malignancies with BCMA- and CD19-directed genetically modified autologous T cell immunotherapies (5.8).

RECENT MAJOR CHANGES

Boxed Warning | 04/2024
Dosage and Administration (2.2, 2.3) | 06/2025
Warnings and Precautions (5.1, 5.2) | 06/2025
Warnings and Precautions, YESCARTA and TECARTUS REMS (5.3) | Removed 06/2025
Warnings and Precautions, Secondary Malignancies (5.8) | 04/2024
Warnings and Precautions, Effects on Ability to Drive and Use Machines (5.10) | Removed 06/2025

1 INDICATIONS AND USAGE

TECARTUS is a CD19-directed genetically modified autologous T cell immunotherapy indicated for the treatment of:

- Adult patients with relapsed or refractory mantle cell lymphoma (MCL).
  This indication is approved under accelerated approval based on overall response rate and durability of response. Continued approval for this indication may be contingent upon verification and description of clinical benefit in a confirmatory trial.
- Adult patients with relapsed or refractory B-cell precursor acute lymphoblastic leukemia (ALL).

2 DOSAGE AND ADMINISTRATION

For autologous use only. For intravenous use only.

- Do NOT use a leukodepleting filter.
- Administer a lymphodepleting regimen of cyclophosphamide and fludarabine before infusion of TECARTUS. (2.2)
- Verify the patient's identity prior to infusion. (2.2)
- Premedicate with acetaminophen and diphenhydramine. (2.2)
- Confirm availability of tocilizumab prior to infusion. (2.2, 5.1)
- Dosing of TECARTUS is based on the number of chimeric antigen receptor (CAR)-positive viable T cells. (2.1)
- MCL: dose is 2 × 10^6 CAR-positive viable T cells per kg body weight, with a maximum of 2 × 10^8 CAR-positive viable T cells. (2.1)
- ALL: dose is 1 × 10^6 CAR-positive viable T cells per kg body weight, with a maximum of 1 × 10^8 CAR-positive viable T cells. (2.1)

3 DOSAGE FORMS AND STRENGTHS

- TECARTUS is available as a cell suspension for infusion.
- MCL: Comprises a suspension of 2 × 10^6 CAR-positive viable T cells per kg of body weight, with a maximum of 2 × 10^8 CAR-positive viable T cells in approximately 68 mL. (3)
- ALL: Comprises a suspension of 1 × 10^6 CAR-positive viable T cells per kg of body weight, with a maximum of 1 × 10^8 CAR-positive viable T cells in approximately 68 mL. (3)

4 CONTRAINDICATIONS

- None. (4)

5 WARNINGS AND PRECAUTIONS

- Hemophagocytic Lymphohistiocytosis/Macrophage Activation Syndrome: Administer treatment per institutional standards. (5.3)
- Hypersensitivity Reactions: Monitor for hypersensitivity reactions during infusion. (5.4)
- Severe Infections: Monitor patients for signs and symptoms of infection; treat appropriately. (5.5)
- Prolonged Cytopenias: Patients may exhibit Grade 3 or higher cytopenias for several weeks following TECARTUS infusion. Monitor complete blood counts. (5.6)
- Hypogammaglobulinemia: Monitor and provide replacement therapy. (5.7)
- Secondary Malignancies: T cell malignancies have occurred following treatment of hematologic malignancies with BCMA- and CD19-directed genetically modified autologous T cell immunotherapies. In the event that a secondary malignancy occurs after treatment with TECARTUS, contact Kite at 1-844-454-KITE (5483). (5.8)

6 ADVERSE REACTIONS

The most common non-laboratory adverse reactions (incidence greater than or equal to 20%) are:

- MCL: fever, CRS, hypotension, encephalopathy, fatigue, tachycardia, arrhythmia, infection with pathogen unspecified, chills, hypoxia, cough, tremor, musculoskeletal pain, headache, nausea, edema, motor dysfunction, constipation, diarrhea, decreased appetite, dyspnea, rash, insomnia, pleural effusion, and aphasia. (6.1)
- ALL: fever, CRS, hypotension, encephalopathy, tachycardia, nausea, chills, headache, fatigue, febrile neutropenia, diarrhea, musculoskeletal pain, hypoxia, rash, edema, tremor, infection with pathogen unspecified, constipation, decreased appetite, and vomiting. (6.1).

To report SUSPECTED ADVERSE REACTIONS, contact Kite at 1-844-454-KITE (5483) or FDA at 1-800-FDA-1088 or www.fda.gov/medwatch.

FULL PRESCRIBING INFORMATION

WARNING: CYTOKINE RELEASE SYNDROME, NEUROLOGIC TOXICITIES, and SECONDARY HEMATOLOGICAL MALIGNANCIES

- Cytokine Release Syndrome (CRS), including life-threatening reactions, occurred in patients receiving TECARTUS. Do not administer TECARTUS to patients with active infection or inflammatory disorders. Treat severe or life-threatening CRS with tocilizumab or tocilizumab and corticosteroids [see Dosage and Administration (2.2, 2.3), Warnings and Precautions (5.1)].
- Neurologic toxicities, including life-threatening reactions, occurred in patients receiving TECARTUS, including concurrently with CRS or after CRS resolution. Monitor for neurologic toxicities after treatment with TECARTUS. Provide supportive care and/or corticosteroids, as needed [see Dosage and Administration (2.2, 2.3), Warnings and Precautions (5.2)].
- T cell malignancies have occurred following treatment of hematologic malignancies with BCMA- and CD19-directed genetically modified autologous T cell immunotherapies [see Warnings and Precautions (5.8)].

1 INDICATIONS AND USAGE

TECARTUS is a CD19-directed genetically modified autologous T cell immunotherapy indicated for the treatment of:

1.1 Mantle Cell Lymphoma

Adult patients with relapsed or refractory mantle cell lymphoma (MCL).

This indication is approved under accelerated approval based on overall response rate and durability of response [see Clinical Studies (14)]. Continued approval for this indication may be contingent upon verification and description of clinical benefit in a confirmatory trial.

1.2 Acute Lymphoblastic Leukemia

Adult patients with relapsed or refractory B-cell precursor acute lymphoblastic leukemia (ALL).

2 DOSAGE AND ADMINISTRATION

For autologous use only. For intravenous use only.

Each single infusion bag of TECARTUS contains a suspension of chimeric antigen receptor (CAR)-positive T cells in approximately 68 mL.

2.1 Dose

Recommended Dosage for MCL

The target dose is 2 × 10^6 CAR-positive viable T cells per kg body weight, with a maximum of 2 × 10^8 CAR-positive viable T cells.

Recommended Dosage for ALL

The target dose is 1 × 10^6 CAR-positive viable T cells per kg body weight, with a maximum of 1 × 10^8 CAR-positive viable T cells.

2.2 Administration

TECARTUS is for autologous use only. The patient's identity must match the patient identifiers on the TECARTUS cassette and infusion bag. Do not infuse TECARTUS if the information on the patient-specific label does not match the intended patient.

Preparing Patient for TECARTUS Infusion

Confirm availability of TECARTUS prior to starting the lymphodepleting chemotherapy regimen.

Pre-treatment

- MCL: Administer a lymphodepleting chemotherapy regimen of cyclophosphamide 500 mg/m^2 intravenously and fludarabine 30 mg/m^2 intravenously on each of the fifth, fourth, and third day before infusion of TECARTUS.
- ALL: Administer a lymphodepleting chemotherapy regimen of fludarabine 25 mg/m^2 intravenously over 30 minutes on the fourth, third, and second day and administer cyclophosphamide 900 mg/m^2 over 60 minutes on the second day before infusion of TECARTUS.

Premedication

- Premedicate with acetaminophen and diphenhydramine or another H1-antihistamine approximately 30 to 60 minutes prior to TECARTUS infusion.
- Avoid prophylactic use of systemic corticosteroids as it may interfere with the activity of TECARTUS.

Preparation of TECARTUS for infusion

Coordinate the timing of TECARTUS thaw and infusion. Confirm the infusion time in advance, and adjust the start time of TECARTUS thaw such that TECARTUS will be available for infusion when the patient is ready.

- Confirm patient identity: Prior to TECARTUS preparation, match the patient's identity with the patient identifiers on the TECARTUS cassette.
- Do not remove the TECARTUS infusion bag from the cassette if the patient information on the cassette label does not match the intended patient.
- Once patient identity is confirmed, remove the TECARTUS infusion bag from the cassette and check that the patient information on the cassette label matches the patient information on the bag label.
- Inspect the infusion bag for any breaches of container integrity such as breaks or cracks before thawing. If the bag is compromised, follow the local guidelines (or call Kite at 1-844-454-KITE).
- Place the infusion bag inside a second sterile bag per local guidelines.
- Thaw the infusion bag at approximately 37°C using either a water bath or dry-thaw method until there is no visible ice in the infusion bag.
- Gently mix the contents of the bag to disperse clumps of cellular material. If visible cell clumps remain, continue to gently mix the contents of the bag. Small clumps of cellular material should disperse with gentle manual mixing. Do not wash, spin down, and/or re-suspend TECARTUS in new media prior to infusion.
- Once thawed, TECARTUS should be administered within 30 minutes but may be stored at room temperature (20°C to 25°C) for up to three hours.

Administration

- For autologous use only.
- Confirm that tocilizumab and emergency equipment are available prior to infusion and during the recovery period.
- Do NOT use a leukodepleting filter.
- Central venous access is recommended for the administration of TECARTUS.
- Confirm that the patient's identity matches the patient identifiers on the TECARTUS infusion bag.
- Prime the tubing with normal saline prior to infusion.
- Infuse the entire contents of the TECARTUS bag within 30 minutes by either gravity or a peristaltic pump. TECARTUS is stable at room temperature for up to three hours after thaw.
- Gently agitate the TECARTUS bag during infusion to prevent cell clumping.
- After the entire contents of the TECARTUS bag are infused, rinse the tubing with normal saline at the same infusion rate to ensure all product is delivered.

TECARTUS contains human blood cells that are genetically modified with replication-incompetent retroviral vector. Follow universal precautions and local biosafety guidelines for handling and disposal of TECARTUS to avoid potential transmission of infectious diseases.

Monitoring

- Monitor patients daily for at least 7 days following infusion for signs and symptoms of Cytokine Release Syndrome (CRS) and neurologic events.
- Instruct patients to remain within proximity of a healthcare facility for at least 2 weeks following infusion.
- Advise patients to avoid driving for at least 2 weeks following infusion.

2.3 Management of Severe Adverse Reactions

Cytokine Release Syndrome (CRS)

Identify CRS based on clinical presentation [see Warnings and Precautions (5.1)]. Evaluate for and treat other causes of fever, hypoxia, and hypotension. If CRS is suspected, manage according to the recommendations in Table 1. Patients who experience Grade 2 or higher CRS (e.g., hypotension, not responsive to fluids, or hypoxia requiring supplemental oxygenation) should be monitored with continuous cardiac telemetry and pulse oximetry. For patients experiencing severe CRS, consider performing an echocardiogram to assess cardiac function. For severe or life-threatening CRS, consider intensive care supportive therapy. Physicians may also consider management per current practice guidelines.

Table 1. CRS Grading and Management Guidance
CRS Grade [Lee et al. 2014.] | Tocilizumab | Corticosteroids
Grade 1 Symptoms require symptomatic treatment only (e.g., fever, nausea, fatigue, headache, myalgia, malaise). | If not improving after 24 hours, administer tocilizumab [Refer to tocilizumab Prescribing Information for details.] 8 mg/kg intravenously over 1 hour (not to exceed 800 mg). | Not applicable.
Grade 2 Symptoms require and respond to moderate intervention. Oxygen requirement less than 40% FiO2 or hypotension responsive to fluids or low dose of one vasopressor or Grade 2 organ toxicity. [Refer to Table 2 for management of neurologic toxicity.] | Administer tocilizumab 8 mg/kg intravenously over 1 hour (not to exceed 800 mg). Repeat tocilizumab every 8 hours as needed if not responsive to intravenous fluids or increasing supplemental oxygen. Limit to a maximum of 3 doses in a 24-hour period; maximum total of 4 doses if no clinical improvement in the signs and symptoms of CRS. If improving, discontinue tocilizumab. | Manage per Grade 3 if no improvement within 24 hours after starting tocilizumab. If improving, taper corticosteroids.
Grade 3 Symptoms require and respond to aggressive intervention. Oxygen requirement greater than or equal to 40% FiO2 or hypotension requiring high-dose or multiple vasopressors or Grade 3 organ toxicity or Grade 4 transaminitis. | Per Grade 2 If improving, discontinue tocilizumab. | Administer methylprednisolone 1 mg/kg intravenously twice daily or equivalent dexamethasone (e.g., 10 mg intravenously every 6 hours) until Grade 1, then taper corticosteroids. If improving, manage as Grade 2. If not improving, manage as Grade 4.
Grade 4 Life-threatening symptoms. Requirements for ventilator support or continuous veno-venous hemodialysis (CVVHD), or Grade 4 organ toxicity (excluding transaminitis). | Per Grade 2 If improving, discontinue tocilizumab. | Administer methylprednisolone 1000 mg intravenously per day for 3 days. If improving, taper corticosteroids, and manage as Grade 3. If not improving, consider alternate immunosuppressants.

Neurologic Toxicity

Monitor patients for signs and symptoms of neurologic toxicities/immune effector cell-associated neurotoxicity syndrome (ICANS) (Table 2). Rule out other causes of neurologic symptoms. Patients who experience Grade 2 or higher neurologic toxicities/ICANS should be monitored with continuous cardiac telemetry and pulse oximetry. Provide intensive care supportive therapy for severe or life-threatening neurologic toxicities. Consider non-sedating anti-seizure medicines (e.g., levetiracetam) for seizure prophylaxis for any Grade 2 or higher neurologic toxicities. Physicians may also consider management per current practice guidelines.

Table 2. Neurologic Toxicity/ICANS Grading and Management Guidance
Neurologic Event [Severity based on Common Terminology Criteria for Adverse Events.] | Concurrent CRS | No Concurrent CRS
Grade 1 Examples include: Somnolence – mild drowsiness or sleepiness Confusion – mild disorientation Encephalopathy – mild limiting of ADLs Dysphasia – not impairing ability to communicate | Administer tocilizumab per Table 1 for management of Grade 1 CRS. | Supportive care.
Grade 2 Examples include: Somnolence – moderate limiting instrumental ADLs Confusion – moderate disorientation Encephalopathy – limiting instrumental ADLs Dysphasia moderate impairing ability to communicate spontaneously Seizure(s) | Administer tocilizumab per Table 1 for management of Grade 2 CRS. If not improving within 24 hours after starting tocilizumab, administer dexamethasone 10 mg intravenously every 6 hours until the event is Grade 1 or less, then taper corticosteroids. If improving, discontinue tocilizumab. If still not improving, manage as Grade 3. | Administer dexamethasone 10 mg intravenously every 6 hours until the event is Grade 1 or less. If improving, taper corticosteroids.
Grade 2 Examples include: Somnolence – moderate limiting instrumental ADLs Confusion – moderate disorientation Encephalopathy – limiting instrumental ADLs Dysphasia moderate impairing ability to communicate spontaneously Seizure(s) | Consider non-sedating, anti-seizure medicines (e.g., levetiracetam) for seizure prophylaxis.
Grade 3 Examples include: Somnolence – obtundation or stupor Confusion – severe disorientation Encephalopathy – limiting self-care ADLs Dysphasia – severe receptive or expressive characteristics, impairing ability to read, write, or communicate intelligibly | Administer tocilizumab per Table 1 for management of Grade 2 CRS. In addition, administer dexamethasone 10 mg intravenously with the first dose of tocilizumab and repeat dose every 6 hours. Continue dexamethasone use until the event is Grade 1 or less, then taper corticosteroids. If improving, discontinue tocilizumab and manage as Grade 2. If still not improving, manage as Grade 4. | Administer dexamethasone 10 mg intravenously every 6 hours. Continue dexamethasone use until the event is Grade 1 or less, then taper corticosteroids. If not improving, manage as Grade 4.
Grade 3 Examples include: Somnolence – obtundation or stupor Confusion – severe disorientation Encephalopathy – limiting self-care ADLs Dysphasia – severe receptive or expressive characteristics, impairing ability to read, write, or communicate intelligibly | Consider non-sedating anti-seizure medicines (e.g., levetiracetam) for seizure prophylaxis.
Grade 4 Life-threatening consequences Urgent intervention indicated Requirement for mechanical ventilation Consider cerebral edema | Administer tocilizumab per Table 1 for management of Grade 2 CRS. Administer methylprednisolone 1000 mg intravenously per day with first dose of tocilizumab and continue methylprednisolone 1000 mg intravenously per day for 2 more days. If improving, then manage as Grade 3. If not improving, consider alternate immunosuppressants. | Administer methylprednisolone 1000 mg intravenously per day for 3 days. If improving, then manage as Grade 3. If not improving, consider alternate immunosuppressants.
Grade 4 Life-threatening consequences Urgent intervention indicated Requirement for mechanical ventilation Consider cerebral edema | Consider non-sedating anti-seizure medicines (e.g., levetiracetam) for seizure prophylaxis.
Abbreviation: ADLs, activities of daily living.

3 DOSAGE FORMS AND STRENGTHS

TECARTUS is available as a cell suspension for infusion.

- MCL: A single dose of TECARTUS contains 2 × 10^6 CAR-positive viable T cells per kg of body weight [maximum of 2 × 10^8 CAR-positive viable T cells (for patients 100 kg and above)] in approximately 68 mL suspension in an infusion bag [see How Supplied/Storage and Handling (16)].
- ALL: A single dose of TECARTUS contains 1 × 10^6 CAR-positive viable T cells per kg of body weight [maximum of 1 × 10^8 CAR-positive viable T cells (for patients 100 kg and above)] in approximately 68 mL suspension in an infusion bag [see How Supplied/Storage and Handling (16)].

4 CONTRAINDICATIONS

None.

5 WARNINGS AND PRECAUTIONS

5.1 Cytokine Release Syndrome

CRS, including fatal or life-threatening reactions, occurred following treatment with TECARTUS. CRS occurred in 91% (75/82) of patients with MCL, including ≥ Grade 3 (Lee grading system^1) CRS in 18% of patients. Among the patients with MCL who died after receiving TECARTUS, one patient had a fatal CRS event. The median time to onset of CRS was three days (range: 1 to 13 days) and the median duration of CRS was ten days (range: 1 to 50 days) for patients with MCL. CRS occurred in 92% (72/78) of patients with ALL, including ≥ Grade 3 (Lee grading system^1) CRS in 26% of patients. Three patients with ALL had ongoing CRS events at the time of death. The median time to onset of CRS was five days (range: 1 to 12 days) and the median duration of CRS was eight days (range: 2 to 63 days) for patients with ALL.

The incidence of CRS (first occurrence) within the first 7 days after TECARTUS infusion was 83% (68/82) in patients with MCL and 90% (70/78) in patients with ALL. In all patients combined (MCL/ALL), the incidence of first CRS (first occurrence) within the first 7 days after TECARTUS infusion was 86% (138/160).

Among patients with CRS, the key manifestations (>10%) were similar in MCL and ALL and included fever (93%), hypotension (62%), tachycardia (59%), chills (32%), hypoxia (31%), headache (21%), fatigue (20%), and nausea (13%). Serious events associated with CRS in MCL and ALL combined (≥ 2%) included hypotension, fever, hypoxia, tachycardia, and dyspnea [see Adverse Reactions (6)].

Confirm that a minimum of two doses of tocilizumab are available for each patient prior to infusion of TECARTUS. Monitor patients daily for at least 7 days following infusion for signs and symptoms of CRS. Monitor patients for signs or symptoms of CRS for 2 weeks after infusion. Counsel patients to seek immediate medical attention should signs or symptoms of CRS occur at any time [see Patient Counseling Information (17)]. At the first sign of CRS, institute treatment with supportive care, tocilizumab, or tocilizumab and corticosteroids as indicated [see Dosage and Administration (2.3)].

5.2 Neurologic Toxicities

Neurologic toxicities (including ICANS) that were fatal or life-threatening, occurred following treatment with TECARTUS. Neurologic events occurred in 81% (66/82) of patients with MCL, including ≥ Grade 3 in 37% of patients. The median time to onset for neurologic events was six days (range: 1 to 32 days) with a median duration of 21 days (range: 2 to 454 days) in patients with MCL. Neurologic events occurred in 87% (68/78) of patients with ALL, including ≥ Grade 3 in 35% of patients. The median time to onset for neurologic events was 7 days (range: 1 to 51 days) with a median duration of 15 days (range: 1 to 397 days) in patients with ALL. For patients with MCL, 54 (66%) patients experienced CRS before the onset of neurological events. Five (6%) patients did not experience CRS with neurologic events and eight patients (10%) developed neurological events after the resolution of CRS. Neurologic events resolved for 119 out of 134 (89%) patients treated with TECARTUS. Nine patients (three patients with MCL and six patients with ALL) had ongoing neurologic events at the time of death. For patients with ALL, neurologic events occurred before, during, and after CRS in 4 (5%), 57 (73%), and 8 (10%) of patients; respectively. Three patients (4%) had neurologic events without CRS. The onset of neurologic events can be concurrent with CRS, following resolution of CRS or in the absence of CRS.

The incidence of neurologic events (first occurrence) within the first 7 days after TECARTUS infusion was 56% (46/82) in patients with MCL and 55% (43/78) in patients with ALL. In all patients combined (MCL/ALL) the incidence of neurologic events (first occurrence) within the first 7 days after TECARTUS infusion was 56% (89/160). Ninety-one percent of all treated patients experienced the first CRS or neurological event within the first 7 days after TECARTUS infusion.

The most common neurologic events (>10%) were similar in MCL and ALL and included encephalopathy (57%), headache (37%), tremor (34%), confusional state (26%), aphasia (23%), delirium (17%), dizziness (15%), anxiety (14%), and agitation (12%). Serious events (≥ 2%) including encephalopathy, aphasia, confusional state, and seizures occurred after treatment with TECARTUS.

Monitor patients daily for at least 7 days following infusion for signs and symptoms of neurologic toxicity/ICANS. Monitor patients for signs or symptoms of neurologic toxicities for 2 weeks after infusion and treat promptly [see Dosage and Administration (2.3)]. Advise patients to avoid driving for at least 2 weeks following infusion.

5.3 Hemophagocytic Lymphohistiocytosis/Macrophage Activation Syndrome

Hemophagocytic Lymphohistiocytosis/Macrophage Activation Syndrome (HLH/MAS), including life-threatening reactions, occurred following treatment with TECARTUS. HLH/MAS occurred in 4% (3/78) of patients with ALL. Two patients experienced Grade 3 events and 1 patient experienced a Grade 4 event. The median time to onset for HLH/MAS was 8 days (range: 6 to 9 days) with a median duration of 5 days (range: 2 to 8 days). All three patients with HLH/MAS had concurrent CRS symptoms and neurologic events after TECARTUS infusion. Treatment of HLH/MAS should be administered per institutional standards.

5.4 Hypersensitivity Reactions

Serious hypersensitivity reactions, including anaphylaxis, may occur due to dimethyl sulfoxide (DMSO) or residual gentamicin in TECARTUS.

5.5 Severe Infections

Severe or life-threatening infections occurred in patients after TECARTUS infusion. Infections (all grades) occurred in 56% (46/82) of patients with MCL and 44% (34/78) of patients with ALL. Grade 3 or higher infections, including bacterial, viral, and fungal infections, occurred in 30% of patients with ALL and MCL. TECARTUS should not be administered to patients with clinically significant active systemic infections. Monitor patients for signs and symptoms of infection before and after TECARTUS infusion and treat appropriately. Administer prophylactic antimicrobials according to local guidelines.

Febrile neutropenia was observed in 6% of patients with MCL and 35% of patients with ALL after TECARTUS infusion and may be concurrent with CRS. The febrile neutropenia in 27 (35%) of patients with ALL includes events of "febrile neutropenia" (11 (14%)) plus the concurrent events of "fever" and "neutropenia" (16 (21%)). In the event of febrile neutropenia, evaluate for infection and manage with broad spectrum antibiotics, fluids, and other supportive care as medically indicated.

In immunosuppressed patients, life-threatening and fatal opportunistic infections have been reported. The possibility of rare infectious etiologies (e.g., fungal and viral infections such as HHV-6 and progressive multifocal leukoencephalopathy) should be considered in patients with neurologic events and appropriate diagnostic evaluations should be performed.

Hepatitis B Reactivation

Hepatitis B virus (HBV) reactivation, in some cases resulting in fulminant hepatitis, hepatic failure, and death, can occur in patients treated with drugs directed against B cells. Perform screening for HBV, hepatitis C virus (HCV), and human immunodeficiency virus (HIV) in accordance with clinical guidelines before collection of cells for manufacturing.

5.6 Prolonged Cytopenias

Patients may exhibit cytopenias for several weeks following lymphodepleting chemotherapy and TECARTUS infusion. In patients with MCL, Grade 3 or higher cytopenias not resolved by Day 30 following TECARTUS infusion occurred in 55% (45/82) of patients and included thrombocytopenia (38%), neutropenia (37%), and anemia (17%). In patients with ALL who were responders to TECARTUS treatment, Grade 3 or higher cytopenias not resolved by Day 30 following TECARTUS infusion occurred in 20% (7/35) of the patients and included neutropenia (12%) and thrombocytopenia (12%); Grade 3 or higher cytopenias not resolved by Day 60 following TECARTUS infusion occurred in 11% (4/35) of the patients and included neutropenia (9%) and thrombocytopenia (6%). Monitor blood counts after TECARTUS infusion.

5.7 Hypogammaglobulinemia

B cell aplasia and hypogammaglobulinemia can occur in patients receiving treatment with TECARTUS. Hypogammaglobulinemia was reported in 16% (13/82) of patients with MCL and 9% (7/78) of patients with ALL. Monitor immunoglobulin levels after treatment with TECARTUS and manage using infection precautions, antibiotic prophylaxis, and immunoglobulin replacement.

The safety of immunization with live viral vaccines during or following TECARTUS treatment has not been studied. Vaccination with live virus vaccines is not recommended for at least six weeks prior to the start of lymphodepleting chemotherapy, during TECARTUS treatment, and until immune recovery following treatment with TECARTUS.

5.8 Secondary Malignancies

Patients treated with TECARTUS may develop secondary malignancies. T cell malignancies have occurred following treatment of hematologic malignancies with BCMA- and CD19-directed genetically modified autologous T cell immunotherapies. Mature T cell malignancies, including CAR-positive tumors, may present as soon as weeks following infusion, and may include fatal outcomes. [see Boxed Warning, Adverse Reactions (6.3), Patient Counseling Information (17)].

Monitor life-long for secondary malignancies. In the event that a secondary malignancy occurs, contact Kite at 1-844-454-KITE (5483) to obtain instructions on patient samples to collect for testing.

6 ADVERSE REACTIONS

The following clinically significant adverse reactions are described elsewhere in the labeling:

- Cytokine Release Syndrome [see Warnings and Precautions (5.1)]
- Neurologic Toxicities [see Warnings and Precautions (5.2)]
- Hemophagocytic Lymphohistiocytosis/Macrophage Activation Syndrome [see Warnings and Precautions (5.3)]
- Hypersensitivity Reactions [see Warnings and Precautions (5.4)]
- Severe Infections [see Warnings and Precautions (5.5)]
- Prolonged Cytopenias [see Warnings and Precautions (5.6)]
- Hypogammaglobulinemia [see Warnings and Precautions (5.7)]

6.1 Clinical Trials Experience

Because clinical trials are conducted under widely varying conditions, adverse reaction rates observed in the clinical trials of a drug cannot be directly compared to rates in the clinical trials of another drug and may not reflect the rates observed in practice.

Patients with Relapsed/Refractory Mantle Cell Lymphoma (MCL)

The safety of TECARTUS was evaluated in a Phase 2 single-arm clinical study (ZUMA-2) in which a total of 82 patients with relapsed/refractory MCL received a single dose of CAR-positive viable T cells (2 × 10^6 or 0.5 × 10^6 anti-CD19 CAR T cells/kg) that was weight-based [see Clinical Studies (14.1)].

The most common adverse reactions (incidence ≥ 20%) were fever, CRS, hypotension, encephalopathy, fatigue, tachycardia, arrhythmia, infection with pathogen unspecified, chills, hypoxia, cough, tremor, musculoskeletal pain, headache, nausea, edema, motor dysfunction, constipation, diarrhea, decreased appetite, dyspnea, rash, insomnia, pleural effusion, and aphasia. Serious adverse reactions occurred in 66% of patients. The most common serious adverse reactions (> 2%) were encephalopathy, fever, infection with pathogen unspecified, CRS, hypoxia, aphasia, renal insufficiency, pleural effusion, respiratory failure, bacterial infections, dyspnea, fatigue, arrhythmia, tachycardia, and viral infections.

The most common (≥ 10%) Grade 3 or higher reactions were anemia, neutropenia, thrombocytopenia, hypotension, hypophosphatemia, encephalopathy, leukopenia, hypoxia, fever, hyponatremia, hypertension, infection with pathogen unspecified, pneumonia, hypocalcemia, and lymphopenia.

Table 3 summarizes the adverse reactions that occurred in at least 10% of patients treated with TECARTUS and Table 4 describes the laboratory abnormalities of Grade 3 or 4 that occurred in at least 10% of patients.

Table 3. Summary of Adverse Reactions Observed in at Least 10% of Patients Treated with TECARTUS in ZUMA-2 (N=82)
Adverse Reaction | Any Grade (%) | Grade 3 or Higher (%)
Blood and Lymphatic System Disorders
Coagulopathy [Coagulopathy includes coagulopathy, disseminated intravascular coagulation, international normalized ratio increased.] | 10 | 2
Cardiac Disorders
Tachycardias [Tachycardias includes tachycardia, sinus tachycardia.] | 45 | 0
Bradycardias [Bradycardias includes bradycardia, sinus bradycardia.] | 10 | 0
Non-ventricular Arrhythmias [Non-ventricular arrhythmias includes atrial fibrillation, atrial flutter, cardiac flutter, palpitations, supraventricular tachycardia.] | 10 | 4
Gastrointestinal Disorders
Nausea | 35 | 1
Constipation | 29 | 0
Diarrhea | 28 | 5
Abdominal pain [Abdominal pain includes abdominal pain, abdominal pain lower, abdominal pain upper, abdominal tenderness.] | 17 | 0
Oral pain [Oral pain includes oral pain, gingival pain, lip pain, oral mucosal erythema, oropharyngeal pain.] | 16 | 0
Vomiting [Vomiting includes vomiting, retching.] | 13 | 0
Dysphagia | 10 | 2
General Disorders and Administration Site Conditions
Fever | 94 | 15
Fatigue [Fatigue includes fatigue, lethargy, malaise.] | 48 | 1
Chills | 41 | 0
Edema [Edema includes eyelid edema, face edema, generalized edema, localised edema, edema, edema peripheral, periorbital edema, peripheral swelling, scrotal edema, swelling face.] | 35 | 2
Pain [Pain includes pain, allodynia, dysaesthesia, ear pain, facial pain, non-cardiac chest pain.] | 17 | 2
Immune System Disorders
Cytokine release syndrome | 91 | 18
Hypogammaglobulinemia [Hypogammaglobulinemia includes hypogammaglobulinemia, blood immunoglobulin G decreased.] | 16 | 1
Infections and Infestations
Infection with pathogen unspecified | 43 | 24
Viral infections | 18 | 4
Bacterial infections | 13 | 6
Metabolism and Nutrition Disorders
Decreased appetite | 26 | 0
Musculoskeletal and Connective Tissue Disorders
Musculoskeletal pain [Musculoskeletal pain includes musculoskeletal pain, arthralgia, back pain, bone pain, dysarthria, flank pain, groin pain, myalgia, neck pain, pain in extremity.] | 37 | 2
Motor dysfunction [Motor dysfunction includes asthenia, intensive care acquired weakness, mobility decreased, muscle twitching, muscular weakness, myopathy.] | 17 | 4
Nervous System Disorders
Encephalopathy [Encephalopathy includes encephalopathy, altered state of consciousness, amnesia, balance disorder, cognitive disorder, confusional state, disturbance in attention, dysgraphia, dyskinesia, memory impairment, mental status changes, neurotoxicity, somnolence.] | 51 | 24
Tremor | 38 | 2
Headache [Headache includes headache, migraine.] | 35 | 1
Aphasia [Aphasia includes aphasia, communication disorder.] | 20 | 7
Dizziness [Dizziness includes dizziness, presyncope, syncope.] | 18 | 6
Neuropathy [Neuropathy includes hyperaesthesia, neuropathy peripheral, paraesthesia, paraesthesia oral.] | 13 | 2
Psychiatric Disorders
Insomnia | 21 | 0
Delirium [Delirium includes delirium, agitation, disorientation, hallucination, hypomania, irritability, nervousness, personality change.] | 18 | 5
Anxiety | 16 | 0
Renal and Urinary Disorders
Renal insufficiency [Renal insufficiency includes acute kidney injury, blood creatinine increased.] | 18 | 9
Urine output decreased [Urine output decreased includes urine output decreased, urinary retention.] | 11 | 1
Respiratory, Thoracic and Mediastinal Disorders
Hypoxia | 40 | 20
Cough [Cough includes cough, upper-airway cough syndrome.] | 38 | 0
Dyspnea [Dyspnea includes dyspnea, dyspnea exertional.] | 24 | 6
Pleural effusion | 21 | 5
Skin and Subcutaneous Tissue Disorders
Rash [Rash includes rash, erythema, rash erythematous, rash maculo-papular, rash pustular.] | 22 | 4
Vascular Disorders
Hypotension [Hypotension includes hypotension, orthostatic hypotension.] | 57 | 27
Hypertension | 18 | 11
Thrombosis [Thrombosis includes thrombosis, deep vein thrombosis, embolism, pulmonary embolism.] | 17 | 4

Other clinically important adverse reactions that occurred in less than 10% of patients treated with TECARTUS include the following:

- Gastrointestinal disorders: dry mouth (7%)
- Infections and infestations disorders: fungal infections (9%)
- Metabolism and nutrition disorders: dehydration (6%)
- Nervous system disorders: ataxia (7%), seizure (5%), increased intracranial pressure (2%)
- Respiratory, thoracic and mediastinal disorders: respiratory failure (6%), pulmonary edema (4%)
- Skin and subcutaneous tissue disorders: rash (9%)
- Vascular disorders: hemorrhage (7%)

Table 4. Grade 3 or 4 Laboratory Abnormalities Occurring in ≥ 10% of Patients in ZUMA-2 Following TECARTUS Infusion (N = 82)
 | Grades 3 or 4 (%)
Leukopenia | 95
Neutropenia | 95
Lymphopenia | 86
Thrombocytopenia | 63
Anemia | 55
Hypophosphatemia | 30
Hypocalcemia | 21
Blood uric acid increased | 17
Hyponatremia | 16
Aspartate Aminotransferase increased | 15
Alanine Aminotransferase increased | 15
Hypokalemia | 10

Patients with Relapsed/Refractory B-cell precursor Acute Lymphoblastic Leukemia (ALL)

The safety of TECARTUS was evaluated in a Phase 1/2 open-label, multicenter study (ZUMA-3) in which a total of 78 patients with relapsed/refractory ALL received a single dose of CAR-positive T cells (1 × 10^6 anti-CD19 CAR T cells/kg) that was weight-based [see Clinical Studies (14.2)].

The most common non-laboratory adverse reactions (≥ 20%) were fever, cytokine release syndrome, hypotension, encephalopathy, tachycardia, nausea, chills, headache, fatigue, febrile neutropenia, diarrhea, musculoskeletal pain, hypoxia, rash, edema, tremor, infection with pathogen unspecified, constipation, decreased appetite, and vomiting. The most common serious adverse reactions (≥ 2%) were cytokine release syndrome, febrile neutropenia, hypotension, encephalopathy, fever, infection with pathogen unspecified, hypoxia, tachycardia, bacterial infections, respiratory failure, seizure, diarrhea, dyspnea, fungal infections, viral infections, coagulopathy, delirium, fatigue, hemophagocytic lymphohistiocytosis, musculoskeletal pain, edema, and paraparesis.

The most common (≥ 10%) Grade 3 or 4 reactions were fever, febrile neutropenia, hypotension, encephalopathy, cytokine release syndrome, hypoxia, and infection with pathogen unspecified. Fatal adverse reactions occurred in 5% (4/78) of patients including cerebral edema, sepsis, and fungal pneumonia. Of the 4 patients who had fatal adverse reactions: one patient with fatal pneumonia had pre-existing pneumonia prior to study enrollment, and one patient with fatal sepsis had prolonged cytopenia and immunosuppression from prior therapies and underlying disease.

Table 5 summarizes the adverse reactions (excluding laboratory abnormalities) that occurred in at least 10% of patients treated with TECARTUS and Table 6 describes the laboratory abnormalities of Grade 3 or 4 that occurred in at least 10% of patients.

Table 5. Summary of Adverse Reactions Observed in at Least 10% of Patients Treated with TECARTUS in ZUMA-3 (N=78)
Adverse Reaction | Any Grade (%) | Grade 3 or Higher (%)
Blood and Lymphatic System Disorders
Febrile Neutropenia [Febrile neutropenia includes febrile neutropenia (11 (14%)) and fever occurring concurrently with neutropenia events (16 (21%)).] | 35 | 35
Coagulopathy [Coagulopathy includes blood fibrinogen decreased, coagulopathy, disseminated intravascular coagulation, hypofibrinogenemia, international normalized ratio increased.] | 17 | 5
Cardiac Disorders
Tachycardias [Tachycardias includes sinus tachycardia, tachycardia.] | 63 | 6
Arrhythmia [Arrhythmia includes arrhythmia, arrhythmia supraventricular, atrial fibrillation, atrial flutter, atrial tachycardia, bradycardia, cardiac arrest, electrocardiogram QT prolonged, electrocardiogram T wave inversion, pulseless electrical activity, sinus bradycardia, supraventricular tachycardia, ventricular tachycardia.] | 15 | 1
Gastrointestinal Disorders
Nausea | 41 | 1
Diarrhea | 32 | 6
Abdominal pain [Abdominal pain includes abdominal discomfort, abdominal pain, abdominal pain upper.] | 19 | 0
Constipation | 24 | 0
Vomiting | 21 | 3
General Disorders and Administration Site Conditions
Fever | 96 | 38
Chills | 40 | 0
Edema [Edema includes face edema, fluid overload, generalized edema, edema, edema peripheral, swelling face, tongue edema.] | 29 | 5
Fatigue [Fatigue includes asthenia, cancer fatigue, fatigue, malaise.] | 37 | 1
Pain | 13 | 1
Immune System Disorders
Cytokine release syndrome | 92 | 26
Infections and Infestations
Infection with pathogen unspecified [Infection with pathogen unspecified includes, catheter bacteremia, conjunctivitis, device related infection, mucosal infection, nasopharyngitis, parotitis, pneumonia, sepsis, septic shock, sinusitis, upper respiratory tract infection, urinary tract infection.] | 28 | 22
Bacterial infections [Bacterial infections includes bacteremia, bacterial disease carrier, cellulitis, cellulitis of male external genital organ, clostridial infection, clostridium difficile colitis, clostridium difficile infection, enterococcal bacteremia, enterococcal infection, escherichia bacteremia, escherichia infection, escherichia sepsis, pseudomonas infection, staphylococcal bacteremia, staphylococcal infection, wound infection staphylococcal.] | 15 | 8
Fungal infections [Fungal infections includes bronchopulmonary aspergillosis, candida infection, fungal skin infection, mycotic oral candidiasis, osteomyelitis fungal, pneumocystis jirovecii pneumonia, pneumonia fungal, sinusitis fungal.] | 13 | 5
Metabolism and Nutrition Disorders
Decreased appetite | 22 | 1
Musculoskeletal and Connective Tissue Disorders
Musculoskeletal pain [Musculoskeletal pain includes arthralgia, back pain, bone pain, coccydynia, muscle strain, musculoskeletal chest pain, musculoskeletal pain, myalgia, neck pain, non-cardiac chest pain, pain in extremity.] | 32 | 5
Muscular weakness | 14 | 1
Nervous System Disorders
Encephalopathy [Encephalopathy includes altered state of consciousness, aphasia, cognitive disorder, confusional state, depressed level of consciousness, disturbance in attention, dysarthria, dysgraphia, encephalopathy, immune effector cell-associated neurotoxicity syndrome, memory impairment, mental status changes, slow response to stimuli, slow speech, somnolence, speech disorder.] | 63 | 27
Headache | 38 | 1
Tremor | 29 | 1
Dizziness [Dizziness includes dizziness, syncope.] | 13 | 1
Psychiatric Disorders
Delirium [Delirium includes agitation, delirium, delusion, disorientation, hallucination.] | 18 | 5
Anxiety | 12 | 0
Insomnia | 13 | 0
Respiratory, Thoracic and Mediastinal Disorders
Hypoxia | 31 | 23
Cough [Cough includes cough, productive cough.] | 12 | 0
Dyspnea | 12 | 1
Skin and Subcutaneous Tissue Disorders
Rash [Rash includes catheter site urticaria, dermatitis bullous, drug eruption, pruritus, rash, rash macular, rash maculo-papular, rash pustular, toxic skin eruption, urticaria.] | 31 | 0
Vascular Disorders
Hypotension [Hypotension includes hypotension, orthostatic hypotension.] | 69 | 33
Hemorrhage [Hemorrhage includes conjunctival hemorrhage, contusion, epistaxis, gastric hemorrhage, hematoma, hematoma muscle, hemorrhage intracranial, hemorrhoidal hemorrhage, menorrhagia, petechiae, pulmonary alveolar hemorrhage, retinal hemorrhage, vaginal hemorrhage, vitreous hemorrhage.] | 13 | 4
Hypertension | 13 | 6

Other clinically important adverse reactions that occurred in less than 10% of patients treated with TECARTUS include the following:

- Cardiac disorder: cardiac failure (4%), palpitations (3%)
- Eye disorders: visual impairment (9%)
- Gastrointestinal disorders: dry mouth (6%), dysphagia (4%), oral pain (1%)
- Immune system disorders: hypogammaglobulinemia (9%), hemophagocytic lymphohistiocytosis (4%), drug hypersensitivity (1%)
- Infections and infestations: viral infections (6%)
- Metabolism and nutrition disorders: dehydration (5%), tumor lysis syndrome (1%)
- Musculoskeletal and connective tissue disorders: muscle spasms (4%), musculoskeletal stiffness (3%)
- Nervous system disorders: seizure (8%), ataxia (5%), peripheral neuropathy (4%), myoclonus (3%), paraparesis (3%), brain edema (1%), brain herniation (1%), cauda equina syndrome (1%), monoplegia (1%)
- Renal and urinary disorders: renal impairment (6%)
- Respiratory, thoracic and mediastinal disorders: respiratory failure (9%), pulmonary edema (6%), pleural effusion (4%), pneumonitis (4%)
- Skin and subcutaneous tissue disorders: skin lesion (4%), decubitus ulcer (3%), dry skin (3%), skin ulcer (3%), alopecia (1%), hyperhidrosis (1%), skin hyperpigmentation (1%)
- Vascular disorders: thrombosis (4%)

Table 6. Grade 3 or 4 Laboratory Abnormalities Occurring in ≥ 10% of Patients in ZUMA-3 Following TECARTUS Infusion (N = 78)
 | Grades 3 or 4 (%)
Leukopenia | 99
Neutropenia | 97
Lymphopenia | 96
Thrombocytopenia | 87
Anemia | 77
Hypophosphatemia | 47
Alanine aminotransferase increased | 31
Aspartate aminotransferase increased | 23
Hyperglycemia | 22
Hypocalcemia | 22
Blood uric acid increased | 19
Direct bilirubin increased | 19
Hyponatremia | 19
Hypokalemia | 13
Hyperbilirubinemia | 10

6.2 Immunogenicity

TECARTUS has the potential to induce anti-product antibodies, which has been evaluated using an enzyme-linked immunosorbent assay (ELISA) for the detection of binding antibodies against FMC63, the originating antibody of the anti-CD19 CAR. To date, no anti-CAR T cell antibody immunogenicity has been observed in ZUMA-2. Based on an initial screening assay in ZUMA-2, 17 of 82 patients tested positive for antibodies at any timepoint; however, a confirmatory orthogonal cell-based assay demonstrated that all 17 patients were antibody negative at all timepoints tested. Based on an initial screening assay in ZUMA-3, 16 of 100 patients tested positive for antibodies at any timepoint. Among patients with evaluable samples for confirmatory testing, two patients were confirmed to be antibody-positive after treatment. One of the two patients had a confirmed positive antibody result at Month 6. The second patient had a confirmed antibody result at retreatment Day 28 and Month 3. There is no evidence that the kinetics of initial expansion and persistence of TECARTUS, or the safety or effectiveness of TECARTUS, were altered in these patients.

6.3 Postmarketing Experience

Because adverse events to marketed products are reported voluntarily from a population of uncertain size, it is not always possible to reliably estimate their frequency or establish a causal relationship to product exposure.

The following adverse event has been identified during postmarketing use of TECARTUS.

Immune System Disorders: Infusion related reaction

The following adverse event has been identified during postmarketing use of BCMA- or CD19-directed genetically modified autologous T cell immunotherapies:

Neoplasms: T cell malignancies

8 USE IN SPECIFIC POPULATIONS

8.1 Pregnancy

Risk Summary

There are no available data with TECARTUS use in pregnant women. No animal reproductive and developmental toxicity studies have been conducted with TECARTUS to assess whether TECARTUS can cause fetal harm when administered to a pregnant woman. It is not known if TECARTUS has the potential to be transferred to the fetus. Based on the mechanism of action of TECARTUS, if the transduced cells cross the placenta, they may cause fetal toxicity, including B cell lymphocytopenia. Therefore, TECARTUS is not recommended for women who are pregnant. Pregnancy after TECARTUS infusion should be discussed with the treating physician.

In the U.S. general population, the estimated background risk of major birth defects and miscarriage in clinically recognized pregnancies is 2% – 4% and 15% – 20%, respectively.

8.2 Lactation

Risk Summary

There is no information regarding the presence of TECARTUS in human milk, the effect on the breastfed infant, and the effects on milk production. The developmental and health benefits of breastfeeding should be considered along with the mother's clinical need for TECARTUS and any potential adverse effects on the breastfed infant from TECARTUS or from the underlying maternal condition.

8.3 Females and Males of Reproductive Potential

Pregnancy Testing

Pregnancy status of females with reproductive potential should be verified. Sexually active females of reproductive potential should have a negative pregnancy test prior to starting treatment with TECARTUS.

Contraception

See the Prescribing Information for fludarabine and cyclophosphamide for information on the need for effective contraception in patients who receive the lymphodepleting chemotherapy.

There are insufficient exposure data to provide a recommendation concerning duration of contraception following treatment with TECARTUS.

Infertility

There are no data on the effect of TECARTUS on fertility.

8.4 Pediatric Use

The safety and efficacy of TECARTUS have not been established in pediatric patients.

8.5 Geriatric Use

Of the 82 patients treated with TECARTUS for MCL, 42 (51%) were 65 years of age and over. Of the 78 patients treated with TECARTUS for ALL, 12 (15%) were 65 years of age and over. No overall differences in safety or effectiveness were observed between these patients and younger patients.

11 DESCRIPTION

TECARTUS (brexucabtagene autoleucel) is a CD19-directed genetically modified autologous T cell immunotherapy. To prepare TECARTUS, a patient's own T cells are harvested and genetically modified ex vivo by retroviral transduction to express a chimeric antigen receptor (CAR) comprising a murine anti-CD19 single-chain variable fragment (scFv) linked to CD28 and CD3-zeta co-stimulatory domains. The anti-CD19 CAR T cells are expanded and infused back into the patient, where they can recognize and eliminate CD19-expressing target cells.

TECARTUS is prepared from the patient's peripheral blood mononuclear cells, which are obtained via a standard leukapheresis procedure. The mononuclear cells are enriched for T cells and activated with anti-CD3 and anti-CD28 antibodies in the presence of IL-2, then transduced with a replication-incompetent retroviral vector containing the anti-CD19 CAR transgene. The transduced T cells are expanded in cell culture, washed, formulated into a suspension, and cryopreserved. The manufacture of TECARTUS includes a T cell enrichment step that may reduce the likelihood of circulating CD19-expressing tumor cells in patients' leukapheresis material driving the activation, expansion, and exhaustion of the anti-CD19 CAR T cells during the ex vivo manufacturing process. The product must pass a sterility test before release for shipping as a frozen suspension in a patient-specific infusion bag. The product is thawed prior to infusion [see Dosage and Administration (2.2), How Supplied/Storage and Handling (16)].

In addition to T cells, TECARTUS may contain natural killer (NK) cells. The formulation contains CryoStor (dimethyl sulfoxide [DMSO], final concentration, 5%), sodium chloride (NaCl), and Human Serum Albumin (HSA).

12 CLINICAL PHARMACOLOGY

12.1 Mechanism of Action

TECARTUS, a CD19-directed genetically modified autologous T cell immunotherapy, binds to CD19-expressing cancer cells and normal B cells. Studies demonstrated that following anti-CD19 CAR T cell engagement with CD19-expressing target cells, the CD28 and CD3-zeta co-stimulatory domains activate downstream signaling cascades that lead to T cell activation, proliferation, acquisition of effector functions, and secretion of inflammatory cytokines and chemokines. This sequence of events leads to killing of CD19-expressing cells.

12.2 Pharmacodynamics

After TECARTUS infusion, pharmacodynamic responses were evaluated over a four-week interval by measuring transient elevation of cytokines, chemokines, and other molecules in blood. Levels of cytokines and chemokines such as IL-6, IL-8, IL-10, IL-15, TNF-α, IFN-γ, and sIL2Rα were analyzed. Peak elevation was generally observed within 8 days after infusion, and levels generally returned to baseline within 28 days.

Due to the on-target effect of TECARTUS, a period of B cell aplasia is expected.

12.3 Pharmacokinetics

Following infusion (target dose of 2 × 10^6 anti-CD19 CAR T cells/kg) of TECARTUS in ZUMA-2, anti-CD19 CAR T cells exhibited an initial rapid expansion followed by a decline to near baseline levels by three months. Peak levels of anti-CD19 CAR T cells occurred within the first 15 days after TECARTUS infusion. Following infusion (target dose of 1 × 10^6 anti-CD19 CAR T cells/kg) of TECARTUS in ZUMA-3 (Phase 2), anti-CD19 CAR T cells exhibited an initial rapid expansion followed by a decline to near baseline levels by 6 months. Median anti- CD19 CAR T cell time to peak was 15 days after TECARTUS infusion.

Description of Pharmacokinetics in Adult r/r MCL

The number of anti-CD19 CAR T cells in blood was associated with objective response [complete remission (CR) or partial remission (PR)]. Median peak anti-CD19 CAR T cell level in responders was 102.4 cells/µL (range: 0.2 to 2589.5 cells/µL; n = 51), and in nonresponders was 12.0 cells/µL (range: 0.2 to 1364.0 cells/µL, n = 8). The median AUCDay 0–28 in patients with an objective response was 1487.0 cells/µL∙days (range: 3.8 to 2.77E+04 cells/µL∙days; n = 51) versus 169.5 cells/µL∙days in nonresponders (range: 1.8 to 1.17E+04 cells/µL∙days; n = 8).

Median peak anti-CD19 CAR T cell and AUC0–28 levels in patients who received neither corticosteroids nor tocilizumab (peak: 24.7 cells/µL; AUC0–28: 360.4 cells/µL∙days, n = 18) was similar to patients who received corticosteroids alone (peak: 24.2 cells/µL; AUC0–28: 367.8 cells/µL∙days, n = 2); both groups were lower than patients who received tocilizumab alone (peak: 86.5 cells/µL; AUC0–28: 1188.9 cells/µL∙days, n = 10); the highest exposure was in patients who received both corticosteroids and tocilizumab (peak: 167.2 cells/µL; AUC0–28: 1996.0 cells/µL∙days, n = 37).

Median peak anti-CD19 CAR T cell values were 74.1 cells/µL in patients ≥ 65 years of age (n = 39) and 112.5 cells/µL in patients < 65 years of age (n = 28). Median anti-CD19 CAR T cell AUCDay 0–28 values were 876.5 cells/µL∙day in patients ≥ 65 years of age and 1640.2 cells/µL∙day in patients < 65 years of age.

Gender had no significant impact on AUC Day 0–28 and Cmax of TECARTUS.

Description of Pharmacokinetics in Adult r/r B-cell precursor ALL

Median peak anti-CD19 CAR T cell levels over time by best overall response per independent review was 38.4 cells/µL (range: 1.31 to 1533.4 cells/µL; n = 32) in patients who had overall complete remission (CR+CRi), and 0.5 cells/µL (range: 0.00 to 183.5 cells/µL, n = 17) in patients who had non-complete remission. The median AUC0–28 in patients who had overall complete remission (CR+CRi) was 424.0 cells/µL∙days (range: 14.12 to 19,390.4 cells/µL∙days; n = 32) vs 7.9 cells/µL∙days in patients who had non-complete remission (range: 0.00 to 889.0 cells/µL∙days; n=17).

Median peak anti-CD19 CAR T cell and AUC0–28 levels in patients who received neither corticosteroids nor tocilizumab (peak 5.7 cells/µL; AUC0–28: 60.7 cells/µL∙days, n=11) were higher than patients who received corticosteroids alone (peak: 36.2 cells/ µL; AUC0–28: 423.1 cells/µL∙days, n= 1); both groups were lower than evaluable patients who received tocilizumab alone (peak 11.2 cells/ µL; AUC0–28: 137.4 cells/µL∙days, n=9); the highest exposure was in evaluable patients who received both corticosteroids and tocilizumab (peak: 49.2 cells/µL; AUC0–28: 454.1 cells/ µL∙days, n=34).

Hepatic and renal impairment studies of TECARTUS were not conducted.

13 NONCLINICAL TOXICOLOGY

13.1 Carcinogenesis, Mutagenesis, Impairment of Fertility

No carcinogenicity or genotoxicity studies have been conducted with TECARTUS. No studies have been conducted to evaluate the effects of TECARTUS on fertility.

14 CLINICAL STUDIES

14.1 Relapsed or Refractory Mantle Cell Lymphoma

A single-arm, open-label, multicenter trial (ZUMA-2; NCT02601313) evaluated the efficacy and safety of a single infusion of TECARTUS in adult patients with relapsed or refractory mantle cell lymphoma (MCL) who had previously received anthracycline- or bendamustine-containing chemotherapy, an anti-CD20 antibody, and a Bruton tyrosine kinase inhibitor (BTKi; ibrutinib or acalabrutinib). Eligible patients also had disease progression after their last regimen or refractory disease to their most recent therapy. The study excluded patients with active or serious infections, prior allogeneic hematopoietic stem cell transplant (HSCT), detectable cerebrospinal fluid malignant cells or brain metastases, and any history of central nervous system (CNS) lymphoma or CNS disorders.

Seventy-four patients were leukapheresed, five (7%) of whom did not begin conditioning chemotherapy or receive TECARTUS: three (4%) experienced manufacturing failure, one (1%) died of progressive disease, and one (1%) withdrew from the study. One patient (1%) received lymphodepleting chemotherapy but did not receive TECARTUS due to ongoing active atrial fibrillation. Sixty-eight of the patients who were leukapheresed received a single infusion of TECARTUS, and 60 of these patients were followed for at least six months after their first objective disease response, qualifying them as efficacy-evaluable. Among the 60 efficacy-evaluable patients, 2 × 10^6 CAR-positive viable T cells/kg were administered to 54 (90%). The remaining six (10%) patients received doses of 1.0, 1.6, 1.8, 1.8, 1.9, and 1.9 × 10^6 CAR-positive viable T cells/kg.

Of the 60 efficacy-evaluable patients, the median age was 65 years (range: 38 to 79 years), 51 (85%) were male, and 56 (93%) were white. Most (50 patients; 83%) had stage IV disease. Twenty patients (33% of 60) had baseline bone marrow examinations performed per protocol; of these, ten (50%) were negative, eight (40%) were positive, and two (10%) were indeterminate. The median number of prior therapies among all 60 efficacy-evaluable patients was three (range: two to five). Twenty-six (43%) of the patients had relapsed after or were refractory to autologous HSCT. Twenty-one (35%) had relapsed after their last therapy for MCL, while 36 (60%) were refractory to their last therapy for MCL. Among the 60 efficacy-evaluable patients, 14 (23%) had blastoid MCL. Following leukapheresis and prior to administration of TECARTUS, 21 (35%) of the 60 patients received bridging therapy. Sixteen (27%) were treated with a BTKi, 9 (15%) with a corticosteroid, and 4 (7%) with both a BTKi and a corticosteroid.

Among the 60 efficacy-evaluable patients, the median time from leukapheresis to product delivery was 15 days (range: 11 to 28 days), and the median time from leukapheresis to product infusion was 27 days (range: 19 to 63 days). The protocol-defined lymphodepleting chemotherapy regimen of cyclophosphamide 500 mg/m^2 intravenously and fludarabine 30 mg/m^2 intravenously, both given on each of the fifth, fourth, and third days before TECARTUS infusion, was administered to 53 (88%) of the 60 efficacy-evaluable patients. The remaining seven patients (12%) either received lymphodepletion over four or more days or received TECARTUS four or more days after completing lymphodepletion. All treated patients received TECARTUS infusion on Day 0 and were hospitalized until at least Day 7.

The primary endpoint of objective response rate (ORR) per the Lugano Classification (2014) in patients treated with TECARTUS as determined by an independent review committee is provided in Table 7. The median time to response was 28 days (range: 24 to 92 days) with a median follow-up time for DOR of 8.6 months.

Table 7. Efficacy Results in Adult Patients with Relapsed/Refractory MCL
 | Efficacy-Evaluable Patients N = 60 | All Leukapheresed Patients (ITT) N = 74
Response Rate
Objective Response Rate [Among all responders. DOR is measured from the date of first objective response to the date of progression or death.] , n (%) [95% CI] | 52 (87%) [75, 94] | 59 (80%) [69, 88]
Complete Remission Rate, n (%) [95% CI] | 37 (62%) [48, 74] | 41 (55%) [43, 67]
Partial Remission Rate, n (%) [95% CI] | 15 (25%) [15, 38] | 18 (24%) [15, 36]
Duration of Response (DOR)
Median in months [95% CI] Range [A + sign indicates a censored value.] in months | NR [8.6, NE] 0.0+, 29.2+ | NR [8.6, NE] 0.0+, 29.2+
DOR, if best response is CR, median in months [95% CI] Range in months | NR [13.6, NE] 1.9+, 29.2+ | NR [13.6, NE] 0.0+, 29.2+
DOR, if best response is PR, median in months [95% CI] Range in months | 2.2 [1.5, 5.1] 0.0+, 22.1+ | 2.2 [1.5, 5.1] 0.0+, 22.1+
Median Follow-up for DOR in months [At the time of primary analysis.] | 8.6 | 8.1
CI, confidence interval; CR, complete remission; DOR, duration of response; NE, not estimable; NR, not reached; PR, partial remission.

14.2 Relapsed or Refractory B-cell precursor Acute Lymphoblastic Leukemia

The efficacy of TECARTUS was evaluated in ZUMA-3 (NCT02614066), an open-label, single-arm, multicenter trial in adult patients with relapsed or refractory B-cell precursor acute lymphoblastic leukemia (ALL). Eligible patients were adults with primary refractory ALL, first relapse following a remission lasting ≤ 12 months, relapsed or refractory ALL after second-line or higher therapy, or relapsed or refractory ALL at least 100 days after allogeneic stem cell transplantation (HSCT). The study excluded patients with active or serious infections, active graft-vs-host disease or taking immunosuppressive medications within 4 weeks prior to enrollment, and any history of CNS disorders, including CNS-2 disease with neurologic changes and CNS-3 disease irrespective of neurological changes. Treatment consisted of lymphodepleting chemotherapy (fludarabine 25 mg/m^2 iv daily on Days -4, -3 and -2; cyclophosphamide 900 mg/m^2 iv on Day -2) followed by a single intravenous infusion of TECARTUS at a target dose of 1 × 10^6 anti-CD19 CAR T cells/kg (maximum 1 × 10^8 cells) on Day 0. All treated patients were hospitalized until at least Day 7.

Seventy-one patients were enrolled and leukapheresed; six of these patients did not receive TECARTUS due to manufacturing failure, eight patients were not treated primarily due to adverse events following leukapheresis, two patients underwent leukapheresis and received lymphodepleting chemotherapy but were not treated with TECARTUS, and one patient treated with TECARTUS was inevaluable for efficacy. Among the remaining 54 efficacy-evaluable patients, the median time from leukapheresis to product delivery was 16 days (range: 11 to 39 days) and the median time from leukapheresis to TECARTUS infusion was 29 days (range: 20 to 60 days).

Of the 54 patients who were efficacy-evaluable, the median age was 40 years (range: 19 to 84 years), 61% were male, and 67% were White, 6% were Asian, 2% were Black or African American, and 2% were American Indian or Alaska Native. At enrollment, 46% had refractory relapse, 26% had primary refractory disease, 20% had untreated second or later relapse, and 7% had first untreated relapse. Among prior therapies, 43% of patients were previously treated with allo-SCT, 46% with blinatumomab, and 22% with inotuzumab. Twenty-six percent of patients were Philadelphia chromosome positive (Ph^+). Fifty (93%) patients had received bridging therapy between leukapheresis and lymphodepleting chemotherapy to control disease burden.

The efficacy of TECARTUS was established on the basis of complete remission (CR) within 3 months after infusion and the duration of CR (DOCR). Twenty-eight (51.9%) of the 54 evaluable patients achieved CR, and with a median follow-up for responders of 7.1 months, the median DOCR was not reached (Table 8). The median time to CR was 56 days (range: 25 to 86 days). All efficacy-evaluable patients had potential follow-up for ≥ 10 months with a median actual follow-up time of 12.3 months (range: 0.3 to 22.1 months).

Table 8. Efficacy Results in Adult Patients with Relapsed/Refractory B-cell precursor ALL
 | Efficacy Evaluable Patients [Of the 71 patients that were enrolled (and leukapheresed), 57 patients received lymphodepleting chemotherapy, and 55 patients received TECARTUS. 54 patients were included in the efficacy-evaluable population.] N= 54 | All Leukapheresed Patients N = 71
OCR rate (CR + CRi), n (%) [95% CI] | 35 (64.8) [51, 77] | 36 (50.7) [39, 63]
CR rate, n (%) [95% CI] | 28 (51.9) [37.8, 65.7] | 29 (40.9) [29.3, 53.2]
Duration of Remission, Median in months [95% CI] (Range [A + sign indicates a censored value.] in months) | 13.6 [9.4, NE] (0.03+, 16.07+) | 13.6 [8.7, NE] (0.03+, 16.07+)
DOR, if best response is CR, median in months [95% CI] (Range in months) | NR [9.6, NE] (0.03+, 16.07+) | 13.6 [9.4, NE] (0.03+, 16.07+)
DOR, if best response is CRi, median in months [95% CI] (Range in months) | 8.7 [1.0, NE] (0.03+, 10.15+) | 8.7 [1.0, NE] (0.03+, 10.15+)
Median Follow-up for CR in months | 7.1 (0.03+, 16.1+) | 5.0 (0.03+, 16.1+)
CI, confidence interval; CR, complete remission; CRi, complete remission with incomplete blood count recovery; DOR, duration of remission; NE, not estimable; NR, not reached, OCR, overall complete remission; NE, not estimable

15 REFERENCES

1. Lee DW et al (2014). Current concepts in the diagnosis and management of cytokine release syndrome. Blood. 2014 Jul 10; 124(2): 188–195.

16 HOW SUPPLIED/STORAGE AND HANDLING

TECARTUS is supplied in an infusion bag containing approximately 68 mL of frozen suspension of genetically modified autologous T cells in 5% DMSO and human serum albumin.

Each TECARTUS infusion bag is individually packed in a metal cassette. TECARTUS is supplied in a liquid nitrogen dry shipper.

Indication | Infusion Bag NDC number | Metal Cassette NDC number
MCL | 71287-219-01 | 71287-219-02
ALL | 71287-220-01 | 71287-220-02

STORAGE AND HANDLING

- Match the identity of the patient with the patient identifiers on the cassette and infusion bag upon receipt.
- Store TECARTUS frozen in the vapor phase of liquid nitrogen (less than or equal to -150°C). TECARTUS may be stored for a single time at -80°C (+/- 10°C), for up to 90 days, and not exceeding the labeled expiration date. Do not return TECARTUS to storage in the vapor phase of liquid nitrogen after storage at -80°C.
- Thaw before using [see Dosage and Administration (2)].

17 PATIENT COUNSELING INFORMATION

Advise the patient to read the FDA-approved patient labeling (Medication Guide).

Ensure that patients understand the risk of manufacturing failure (4% in clinical trial). In case of a manufacturing failure, a second manufacturing of TECARTUS may be attempted. In addition, while the patient awaits the product, additional chemotherapy (not the lymphodepletion) may be necessary and may increase the risk of adverse events during the pre-infusion period.

Advise patients to seek immediate attention for any of the following:

- Cytokine Release Syndrome (CRS) - Signs or symptoms associated with CRS, including fever, chills, fatigue, tachycardia, nausea, hypoxia, and hypotension [see Warnings and Precautions (5.1) and Adverse Reactions (6)].
- Neurologic Toxicities - Signs or symptoms associated with neurologic events, including encephalopathy, seizures, changes in level of consciousness, speech disorders, tremors, and confusion [see Warnings and Precautions (5.2) and Adverse Reactions (6)].
- Severe Infections - Signs or symptoms associated with infection [see Warnings and Precautions (5.5) and Adverse Reactions (6)].
- Prolonged Cytopenias - Signs or symptoms associated with bone marrow suppression, including neutropenia, anemia, thrombocytopenia, or febrile neutropenia [see Warnings and Precautions (5.6) and Adverse Reactions (6)].
- Secondary Malignancies - Secondary malignancies, including T cell malignancies, have occurred following treatment with BCMA- and CD19-directed genetically modified autologous T cell immunotherapies [see Boxed Warning, Warnings and Precautions (5.8), Adverse Reactions (6.3)].

Advise patients of the need to:

- Avoid driving for at least 2 weeks.
- Contact Kite at 1-844-454-KITE (5483) if they are diagnosed with a secondary malignancy [see Warnings and Precautions (5.8)].

Manufactured by, Packed by, Distributed by:
Kite Pharma, Inc.
Santa Monica, CA 90404
US License No 2064

© 2025 Kite Pharma, Inc. All Rights Reserved.

125703-GS-007

MEDICATION GUIDE
TECARTUS (pronounced tek-ahr-tuhs)
(brexucabtagene autoleucel)

Read this Medication Guide before you start your TECARTUS treatment. The more you know about your treatment, the more active you can be in your care. Talk with your healthcare provider if you have questions about your health condition or treatment. Reading this Medication Guide does not take the place of talking with your healthcare provider about your treatment.

What is the most important information I should know about TECARTUS?
TECARTUS may cause side effects that are life-threatening and can lead to death. Call or see your healthcare provider or get emergency help right away if you get any of the following:

- Fever (100.4°F/38°C or higher)
- Difficulty breathing
- Chills or shaking chills
- Confusion
- Dizziness or lightheadedness
- Severe nausea, vomiting, or diarrhea
- Fast or irregular heartbeat
- Severe fatigue or weakness

It is important to tell your healthcare provider that you received TECARTUS and to show them your TECARTUS Patient Wallet Card. Your healthcare provider may give you other medicines to treat your side effects.

What is TECARTUS?
TECARTUS is a treatment for adults with mantle cell lymphoma or acute lymphoblastic leukemia. It is used following disease progression while on or after other treatment. TECARTUS is different than other cancer medicines because it is made from your own white blood cells, which have been modified to recognize and attack your lymphoma cells.

Before getting TECARTUS, tell your healthcare provider about all your medical problems, including if you have or have had:

- Neurologic problems (such as seizures, stroke, or memory loss)
- Lung or breathing problems
- Heart problems
- Liver problems
- Kidney problems
- A recent or active infection

Tell your healthcare provider about all the medications you take, including prescription and over-the-counter medicines, vitamins, and herbal supplements.

How will I receive TECARTUS?

- Since TECARTUS is made from your own white blood cells, your blood will be collected by a process called "leukapheresis" (loo-kah-fur-ee-sis), which will concentrate your white blood cells.
- Your blood cells will be sent to a manufacturing center to make your TECARTUS.
- Before you get TECARTUS, you will get three days of chemotherapy to prepare your body.
- When your TECARTUS is ready, your healthcare provider will give it to you through a catheter placed into your vein (intravenous infusion). The infusion usually takes less than 30 minutes.
- You will be monitored daily for at least 7 days after the infusion.
- You should plan to stay close to a healthcare facility for at least 2 weeks after getting TECARTUS. Your healthcare provider will help you with any side effects that may occur.
- You may be hospitalized for side effects. Your healthcare provider will discharge you if your side effects are under control and it is safe for you to leave the hospital.
- Your healthcare provider will want to do blood tests to follow your progress. It is important that you do have your blood tested. If you miss an appointment, call your healthcare provider as soon as possible to reschedule.

What should I avoid after receiving TECARTUS?

- Avoid driving for at least 2 weeks after you get TECARTUS.
- Do not donate blood, organs, tissues, or cells for transplantation.

What are the possible or reasonably likely side effects of TECARTUS?
The most common side effects of TECARTUS include:

- Fever (100.4°F/38°C or higher)
- Low white blood cells (can occur with a fever)
- Low red blood cells
- Low blood pressure (dizziness or lightheadedness, headache, feeling tired, short of breath)
- Fast heartbeat
- Confusion
- Difficulty speaking or slurred speech
- Nausea
- Diarrhea

TECARTUS may increase your risk of getting cancers including certain types of blood cancers. Your healthcare provider should monitor you for this.
These are not all the possible side effects of TECARTUS. Call your healthcare provider about any side effects that concern you. You may report side effects to the FDA at 1-800-FDA-1088.

General information about the safe and effective use of TECARTUS
Medicines are sometimes prescribed for purposes other than those listed in a Medication Guide. If you would like more information about TECARTUS, talk with your healthcare provider. You can ask your healthcare provider for information about TECARTUS that is written for health professionals. You can get additional information by contacting Kite at 1-844-454-KITE (5483) or at www.Tecartus.com.

What are the ingredients in TECARTUS?
Active ingredients: brexucabtagene autoleucel.
Inactive ingredients: albumin (human); DMSO.
TECARTUS is a trademark of Kite Pharma, Inc. All other trademarks referenced herein are the property of their respective owners.
©2025 Kite Pharma, Inc. All Rights Reserved.

This Medication Guide has been approved by the U.S. Food and Drug Administration. Revised: June 2025

PRINCIPAL DISPLAY PANEL - 68 mL Bag Label - Product - MK-00379

NDC 71287-219-01

brexucabtagene autoleucel
TECARTUS®

RX ONLY

FOR AUTOLOGOUS & INTRAVENOUS USE ONLY
No U.S. standard of potency

Dose: One sterile bag for infusion.

Contents: Maximum of 2 x 10^8 autologous anti-CD19 CAR T cells in
approximately 68 mL suspension containing 5% DMSO USP.

Gently mix the contents of the bag
while thawing

See package insert for full prescribing
information and instructions for
administration

Ship and store in vapor phase of liquid
nitrogen ≤ -150°C. Optional one time
storage at -80°C as indicated in the
package insert.

DO NOT USE A
LEUKODEPLETING FILTER

DO NOT IRRADIATE

Manufactured with gentamicin

Not evaluated for infectious
substances

Preservative free

Manufacturer: Kite Pharma, Inc., 2400 Broadway, Santa Monica, CA 90404
Phone: 1-844-454-KITE U.S. Lic. #2064

MK-00379

PRINCIPAL DISPLAY PANEL - 68 mL Cassette Label - Product - MK-00376

NDC 71287-219-02

brexucabtagene autoleucel
TECARTUS®

RX ONLY

FOR AUTOLOGOUS & INTRAVENOUS USE ONLY
No U.S. standard of potency

Dose: One sterile bag for infusion.

Contents: Maximum of 2 x 10^8 autologous anti-CD19 CAR T cells in
approximately 68 mL suspension containing 5% DMSO USP.

Gently mix the contents of
the bag while thawing

See package insert for full
prescribing information and
instructions for administration

Ship and store in vapor phase of
liquid nitrogen ≤ -150°C. Optional
one time storage at -80°C as
indicated in the package insert.

DO NOT USE A
LEUKODEPLETING FILTER

DO NOT IRRADIATE

Manufactured with gentamicin

Not evaluated for infectious
substances

Preservative free

Manufacturer: Kite Pharma, Inc., 2400 Broadway, Santa Monica, CA 90404
Phone: 1-844-454-KITE U.S. Lic. #2064

Kite
A GILEAD Company

MK-00376

PRINCIPAL DISPLAY PANEL - 68 mL Bag Label - Patient - AS-02442

VERIFY
PATIENT ID

brexucabtagene autoleucel
TECARTUS®

Lot: 123456789-0X

Kite Patient ID: 987654321

Expiration Date: YYYY-Mmm-DD

First Name M.I.: FIRST NAME W

Last Name: LAST NAME

DOB: YYYY-Mmm-DD

Hospital Patient ID: 1234567890123456

DIN:

W0123 45 678900
00
9

AS-02442

PRINCIPAL DISPLAY PANEL - 68 mL Cassette Label - Patient - AS-02444

STOP
Confirm patient
ID prior to
infusion

VERIFY
PATIENT ID

brexucabtagene autoleucel
TECARTUS®

Lot: 123456789-0X

Kite Patient ID: 987654321

Expiration Date: YYYY-Mmm-DD

First Name M.I.: FIRST NAME W

Last Name: LAST NAME

DOB: YYYY-Mmm-DD

Hospital Patient ID: 1234567890123456

DIN:

W0123 45 678900
00
9

AS-02444

PRINCIPAL DISPLAY PANEL - 68 mL LN2 Label - AS-02447

brexucabtagene autoleucel
TECARTUS®

Kite Pharma, Inc.
Site: FXX

Expiration Date: YYYY-Mmm-DD

Cell Order: 123456789

LOT: 123456789-01

Ship and store in vapor phase of liquid nitrogen ≤ - 150°C

2400 Broadway, Santa Monica, CA 90404
(XXX) XXX-XXXX

AS-02447

PRINCIPAL DISPLAY PANEL - 68 mL Bag Label - Product - MK-00380

NDC 71287-220-01

brexucabtagene autoleucel
TECARTUS®

RX ONLY

FOR AUTOLOGOUS & INTRAVENOUS USE ONLY
No U.S. standard of potency

Dose: One sterile bag for infusion.

Contents: Maximum of 1 x 10^8 autologous anti-CD19 CAR T cells in
approximately 68 mL suspension containing 5% DMSO USP.

Gently mix the contents of the bag
while thawing

See package insert for full prescribing
information and instructions for
administration

Ship and store in vapor phase of liquid
nitrogen ≤ -150°C. Optional one time
storage at -80°C as indicated in the
package insert.

DO NOT USE A
LEUKODEPLETING FILTER

DO NOT IRRADIATE

Manufactured with gentamicin

Not evaluated for infectious
substances

Preservative free

Manufacturer: Kite Pharma, Inc., 2400 Broadway, Santa Monica, CA 90404
Phone: 1-844-454-KITE U.S. Lic. #2064

MK-00380

PRINCIPAL DISPLAY PANEL - 68 mL Cassette Label - Product - MK-00377

NDC 71287-220-02

brexucabtagene autoleucel
TECARTUS®

RX ONLY

FOR AUTOLOGOUS & INTRAVENOUS USE ONLY
No U.S. standard of potency

Dose: One sterile bag for infusion.

Contents: Maximum of 1 x 10^8 autologous anti-CD19 CAR T cells in
approximately 68 mL suspension containing 5% DMSO USP.

Gently mix the contents of
the bag while thawing

See package insert for full
prescribing information and
instructions for administration

Ship and store in vapor phase of
liquid nitrogen ≤ -150°C. Optional
one time storage at -80°C as
indicated in the package insert.

DO NOT USE A
LEUKODEPLETING FILTER

DO NOT IRRADIATE

Manufactured with gentamicin

Not evaluated for infectious
substances

Preservative free

Manufacturer: Kite Pharma, Inc., 2400 Broadway, Santa Monica, CA 90404
Phone: 1-844-454-KITE U.S. Lic. #2064

Kite
A GILEAD Company

MK-00377

PRINCIPAL DISPLAY PANEL - 68 mL Bag Label - Patient - AS-02532

VERIFY
PATIENT ID

brexucabtagene autoleucel
TECARTUS®

Lot: 123456789-0X

Kite Patient ID: 987654321

Expiration Date: YYYY-Mmm-DD

First Name M.I.: FIRST NAME W

Last Name: LAST NAME

DOB: YYYY-Mmm-DD

Hospital Patient ID: 1234567890123456

DIN:

W0123 45 678900
00
9

AS-02532

PRINCIPAL DISPLAY PANEL - 68 mL Cassette Label - Patient - AS-02534

STOP
Confirm patient
ID prior to
infusion

VERIFY
PATIENT ID

brexucabtagene autoleucel
TECARTUS®

Lot: 123456789-0X

Kite Patient ID: 987654321

Expiration Date: YYYY-Mmm-DD

First Name M.I.: FIRST NAME W

Last Name: LAST NAME

DOB: YYYY-Mmm-DD

Hospital Patient ID: 1234567890123456

DIN:

W0123 45 678900
00
9

AS-02534

PRINCIPAL DISPLAY PANEL - 68 mL LN2 Label - AS-02536

brexucabtagene autoleucel
TECARTUS®

Kite Pharma, Inc.
Site: FXX

Expiration Date: YYYY-Mmm-DD

Cell Order: 123456789

LOT: 123456789-01

Ship and store in vapor phase of liquid nitrogen ≤ -150°C

2400 Broadway, Santa Monica, CA 90404
(XXX) XXX-XXXX

AS-02536